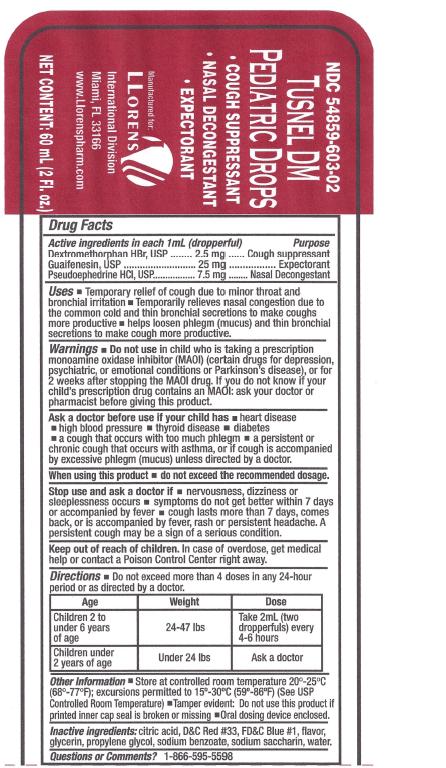 DRUG LABEL: Tusnel DM
NDC: 54859-603 | Form: SOLUTION/ DROPS
Manufacturer: Llorens Pharmaceutical International Division
Category: otc | Type: HUMAN OTC DRUG LABEL
Date: 20251231

ACTIVE INGREDIENTS: GUAIFENESIN 25 mg/1 mL; PSEUDOEPHEDRINE HYDROCHLORIDE 7.5 mg/1 mL; DEXTROMETHORPHAN HYDROBROMIDE 2.5 mg/1 mL
INACTIVE INGREDIENTS: FD&C BLUE NO. 1; CITRIC ACID MONOHYDRATE; GLYCERIN; SODIUM BENZOATE; SACCHARIN SODIUM; PROPYLENE GLYCOL; WATER; D&C RED NO. 33

Llorens-Tusnel DMPedDrops 603

Active Ingredients in each 1 mL (dropperful) Purpose

Dextromethorphan HBr........ 2.5 mg.......................................... Cough suppressant

Guaifenesin........................25mg................................................Expectorant

Pseudoephedrine HCl..........7.5mg..............................................Nasal Decongestant

Uses

- Temporary relief of cough due to minor throat and
  bronchial irritation.
- Temporarily relieves nasal congestion due to
  the common cold and thin bronchial secretions to make coughs
  more productive.
- helps loosen phlegm (mucus) and thin bronchial
  secretions to make cough more productive.

Warnings

Do not use in child who is taking a prescription monoamine oxidaseinhibitor (MAOI) (certain drugs for depression, psychiatric, or emotionalconditions, or Parkinson’s disease), or for 2 weeks after stopping theMAOI drug. If you do not know if your child's prescription drug contains anMAOI, ask a doctor or pharmacist before giving this product.

Ask a doctor before use if your child has

- heart disease
- high blood pressure
- thyroid disease
- diabetes
- a cough that occurs with too much phlegm (mucus)
- a persistent or chronic cough such as occurs with asthma

When using this product

- do not exceed recommended dosage

Stop use and ask a doctor if

- nervousness, dizziness or sleeplessness occurs
- symptoms do not get better within 7 days or accompanied by fever
- cough last more than 7 days, comes back, or is accompanied by fever, rash or persistent headache. A persistent cough could be a sign of a serious condition.

Keep out of reach of children. In case of overdose, get medical help or contact a Poison Control Center right away.

Other information

- store at controlled room temperature 20° - 25° C (68° - 77° F); excursions permitted to 15° - 30° C (59° - 86° F) [See USP Controlled Room Temperature]
- Tamper evident by imprinted heat seal under cap. Do not use if there is evidence of tampering
- Oral dosing device enclosed

INACTIVE INGREDIENT

Inactive ingredients citric acid, D and C Red Number 33,FD and C Blue #1, flavor, glycerin, propylene glycol, sodium benzoate, sodium saccharin, water.

Questions or Comments? 1-866-595-5598

DOSAGE AND ADMINISTRATION

Directions Do not exceed more than 4 doses in any 24-hour periodor as directed by a doctor.

Age | Weight | Dose
Children 2 to under 6 years of age | 24 -47 lbs | Take 2 mL (two dropperfuls) every 4 to 6 hours
Children under 2 years of age | Under 24 lbs | ask a doctor